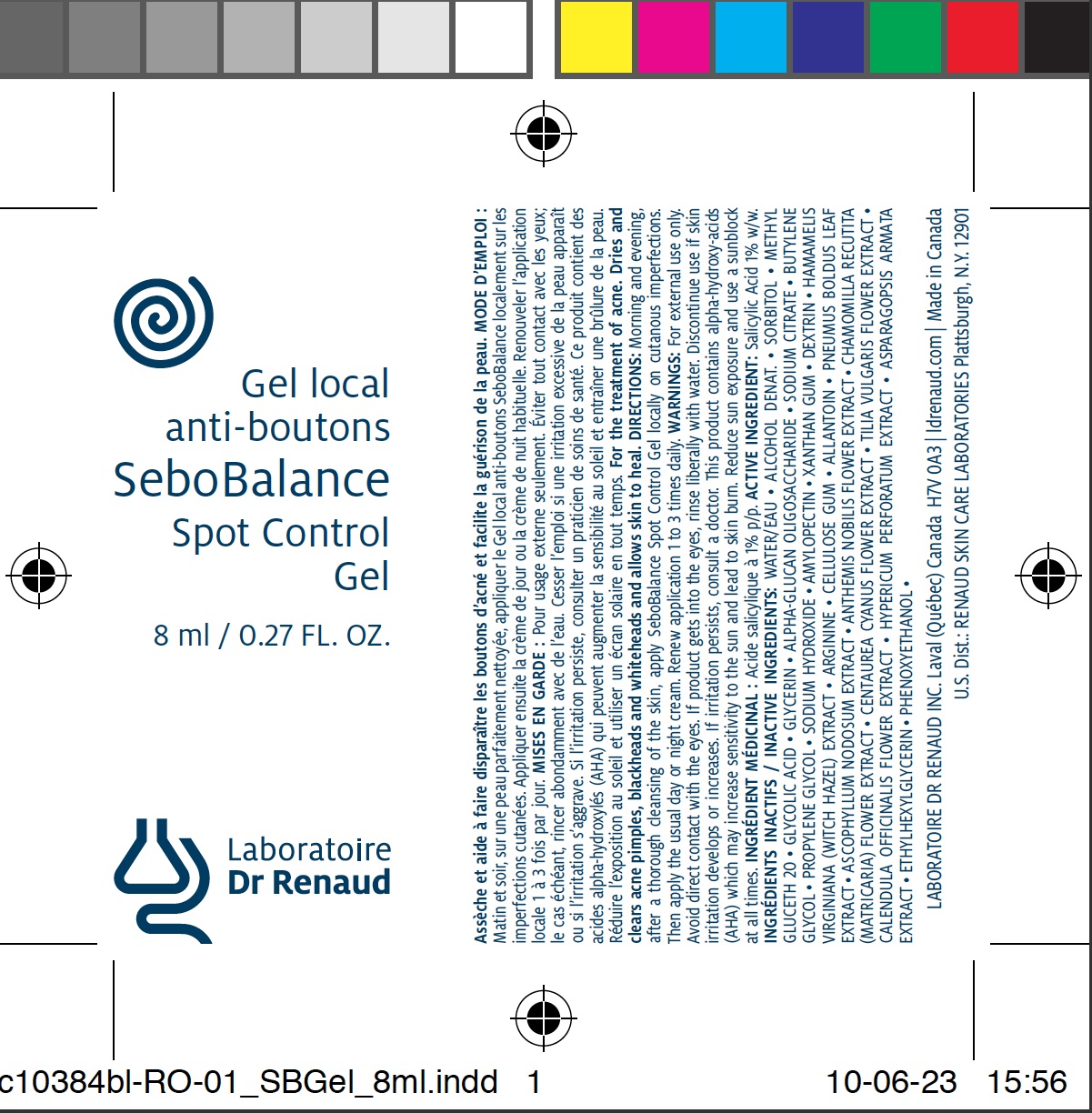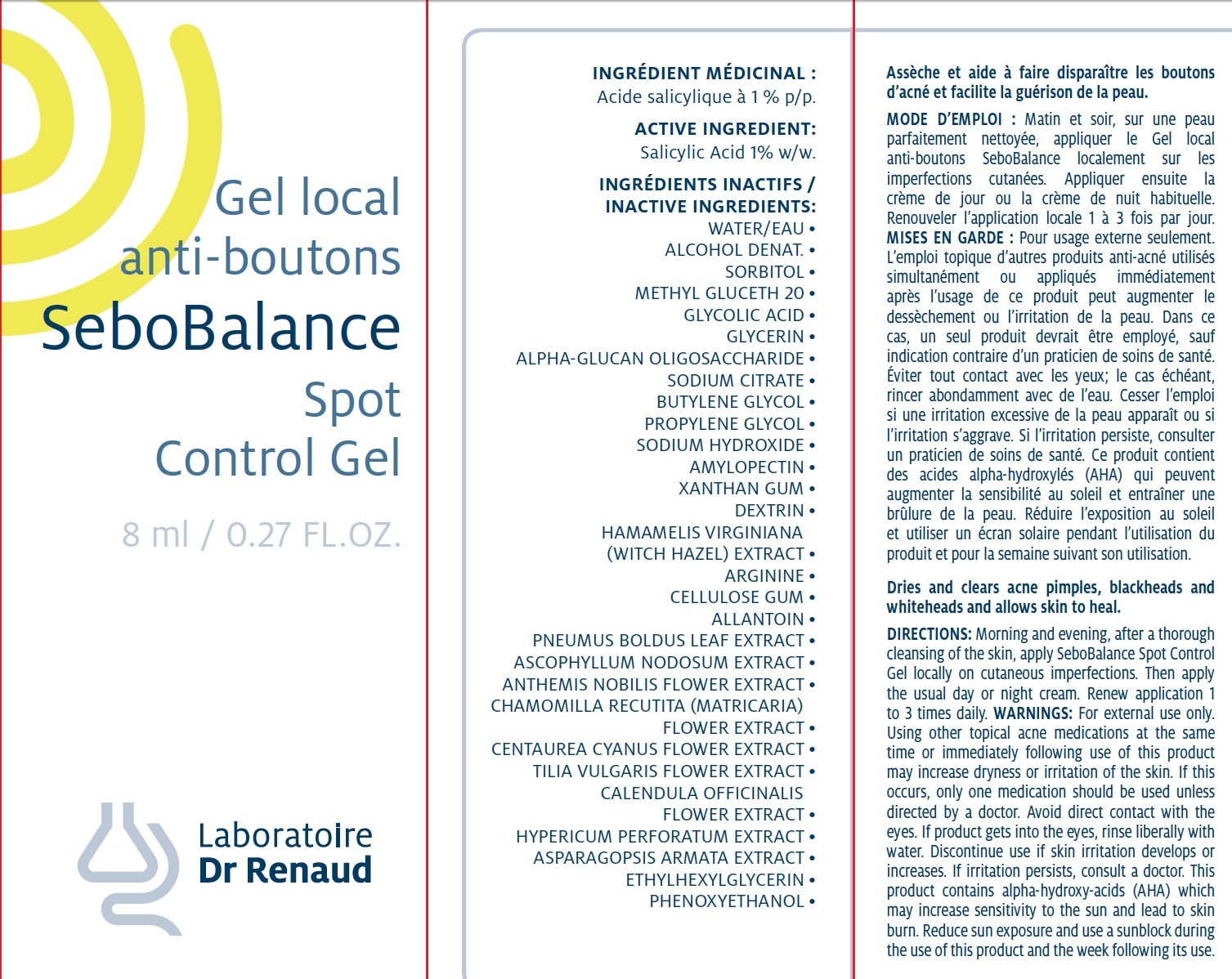 DRUG LABEL: SEBOBALANCE Spot Control 
NDC: 62499-384 | Form: GEL
Manufacturer: Laboratoire Dr. Renaud
Category: otc | Type: HUMAN OTC DRUG LABEL
Date: 20100630

ACTIVE INGREDIENTS: SALICYLIC ACID 1 g/100 g
INACTIVE INGREDIENTS: WATER; ALCOHOL; SORBITOL; METHYL GLUCETH-20; GLYCOLIC ACID; GLYCERIN; SODIUM CITRATE; BUTYLENE GLYCOL; PROPYLENE GLYCOL; PHENOXYETHANOL; SODIUM HYDROXIDE; AMYLOPECTIN; XANTHAN GUM; HAMAMELIS VIRGINIANA ROOT BARK/STEM BARK    ; ARGININE; CARBOXYMETHYLCELLULOSE SODIUM     ; ALLANTOIN; PEUMUS BOLDUS LEAF; ETHYLHEXYLGLYCERIN; ASCOPHYLLUM NODOSUM; CHAMAEMELUM NOBILE FLOWER; CHAMOMILE; CENTAUREA CYANUS FLOWER; TILIA CORDATA FLOWER ; CALENDULA OFFICINALIS FLOWER;  HYPERICUM PERFORATUM  ; ASPARAGOPSIS ARMATA

Drug Facts

ACTIVE INGREDIENT

Salicylic Acid 1% w/w.

INACTIVE INGREDIENTS

WATER/EAU • ALCOHOL DENAT • SORBITOL • METHYL GLUCETH 20 • GLYCOLIC ACID • GLYCERIN •
ALPHA-GLUCAN OLIGOSACCHARIDE • SODIUM CITRATE • BUTYLENE GLYCOL • PROPYLENE GLYCOL • SODIUM HYDROXIDE • AMYLOPECTIN • XANTHAN GUM • DEXTRIN • HAMAMELIS VIRGINIANA (WITCH HAZEL) EXTRACT • ARGININE • CELLULOSE GUM • ALLANTOIN • PEUMUS BOLDUS LEAF EXTRACT • ASCOPHYLLUM NODOSUM EXTRACT • ANTHEMIS NOBILIS FLOWER EXTRACT • CHAMOMILLA RECUTITA (MATRICARIA) FLOWER EXTRACT • CENTAUREA CYANUS FLOWER EXTRACT • TILIA VULGARIS FLOWER EXTRACT • CALENDULA OFFICINALIS FLOWER EXTRACT • HYPERICUM PERFORATUM EXTRACT • ASPARAGOPSIS ARMATA EXTRACT • ETHYLHEXYLGLYCERIN • PHENOXYETHANOL •

PURPOSE

For the treatment of acne. Dries and clears acne pimples, blackheads and whiteheads and allows skin to heal.

DIRECTIONS

Morning and evening, after a thorough cleansing of the skin, apply SeboBalance Spot Control
Gel locally on cutanous imperfections. Then apply the usual day or night cream. Renew application 1 to 3 times daily.

WARNINGS

For external use only. Using other topical acne medications at the same time or immediately following use of this product may increase dryness or irritation of the skin. If this occurs, only one medication should be used unless directed by a doctor. Avoid direct contact with the eyes. If product gets into the eyes, rinse liberally with water. Discontinue use if skin irritation develops or increases. If irritation persists, consult a doctor. This product contains alpha-hydroxy-acids (AHA) which may increase sensitivity to the sun and lead to skin burn. Reduce sun exposure and use a sunblock during the use of this product and the week following its use.

Image of carton label
Image of bottle label

Keep out of reach of children.

INDICATIONS AND USAGE

Enter section text here